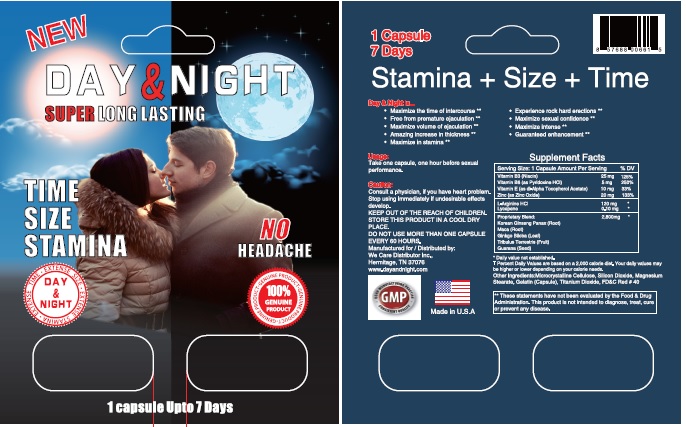 DRUG LABEL: Day and Night Male Sexual Enhancer
NDC: 57688-006 | Form: CAPSULE
Manufacturer: We Care Distributor Inc.
Category: other | Type: DIETARY SUPPLEMENT
Date: 20170428

ACTIVE INGREDIENTS: ARGININE HYDROCHLORIDE 120 mg/1 1; LYCOPENE 0.1 mg/1 1; NIACIN 25 mg/1 1; PYRIDOXINE HYDROCHLORIDE 5 mg/1 1; .ALPHA.-TOCOPHEROL ACETATE, DL- 10 mg/1 1; ZINC OXIDE 20 mg/1 1; PANAX GINSENG LEAF 400 mg/1 1; HYDROLYSED LEPIDIUM MEYENII ROOT (ENZYMATIC) 400 mg/1 1; GINKGO BILOBA ROOT 1000 mg/1 1; TRIBULUS TERRESTRIS ROOT 500 mg/1 1; GUARANA 100 mg/1 1
INACTIVE INGREDIENTS: CELLULOSE, MICROCRYSTALLINE; SILICON DIOXIDE; MAGNESIUM STEARATE; TITANIUM DIOXIDE; FD&C RED NO. 40; GELATIN

Day and Night Male Sexual Enhancer

Directions

Take one capsule 60 minutes prior to sexual activity.

Warning

Consult with a physician to determine if this product is safe for you to use or not. This product contains Herbs, powders and extracts that can have an effect on your health. Do not take this product if you are taking any drug, drinking alcohol, had caffeine or any ingredient that increases energy or affects blood pressure higher or lower. This product is not intended to cure any disease or condition. Do not take if you have any heart issues, high blood pressure, liver issues, or any condition you are being treated for. Consult with your physician before you take this product or any sexual enhancement product.

Caution

Do not take more than one capsule every 24 hours.

These statements have not been evaluated by the Food and Drug Administration. This product is not intended to diagnose, treat, cure, or prevent any diseases. Not intended for use by person under the age of 18.

HEALTH CLAIM

SUPPLEMENT FACT
SERVING SIZE: 1 CAPSULE | AMOUNT PER SERVING | % DAILY VALUE
NIACIN | 25 MG | 125% †
PYRIDOXINE HYDROCHLORIDE | 5 MG | 250% †
DL-ALPHA-TOCOPHEROL ACETATE | 10 MG | 33% †
ZINC OXIDE | 20 MG | 133% †
L-ARGININE HCL | 120 MG | *
LYCOPENE | 0.10 MG | *
PROPRITARY BLEND | 2,800 MG | *
KOREAN GINSENG PANAX (ROOT)
MACA (ROOT)
GINKGO BILOBA (LEAF)
TRIBULUS TERRESTRIS (FRUIT)
GUARANA (SEED)

* Daily Values not established

† Percent daily values established based on 2,000 calories diet.

Other Ingredients

Microcrystalline Cellulose, Silicon Dioxide, Magnesium Stearate, Gelatin, Titanium Dioxide, FD&C Red 40

HEALTH CLAIM

Manufactured by:
VitaCare Pharma LLC
South Plainfield, NJ 07080